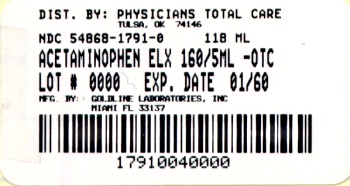 DRUG LABEL: Acetaminophen
NDC: 54868-1791 | Form: LIQUID
Manufacturer: Physicians Total Care, Inc.
Category: otc | Type: HUMAN OTC DRUG LABEL
Date: 20091207

ACTIVE INGREDIENTS: ACETAMINOPHEN 160 mg/5 mL
INACTIVE INGREDIENTS: BENZOIC ACID; CITRIC ACID MONOHYDRATE; D&C RED NO. 33; FD&C RED NO. 40; GLYCERIN; POLYETHYLENE GLYCOL 1450; PROPYLENE GLYCOL; WATER; SODIUM BENZOATE; SORBITOL; SUCROSE

Acetaminophen Oral Solution USP 0182-1473-40

Drug Facts

ACTIVE INGREDIENT

Active ingredient (in each teaspoon (5 mL)) | Purpose
Acetaminophen 160 mg | Pain reliever - fever reducer

Uses

for the temporary relief of minor aches and pains associated with

- a cold or flu
- sore throat
- headache
- toothache
- temporarily reduces fever

Warnings

Sore throat warning:

If sore throat is severe, persists for more than 2 days, is accompanied or followed by fever, headache, rash, nausea, or vomiting, consult a doctor promptly.

Do not use

- with any other product containing acetaminophen
- more than directed (see overdose warning)

Stop use and ask a doctor if

- new symptoms occur
- redness or swelling is present
- pain gets worse or lasts for more than 5 days
- fever gets worse or lasts more than 3 days

PREGNANCY OR BREAST FEEDING

If pregnant or breast-feeding, ask a health professional before use.

Keep out of the reach of children.

Overdose warning:

Taking more than the recommended dose (overdose) may cause liver damage. In case of overdose, get medical help or contact a Poison Control Center right away. Quick medical attention is critical for adults as well as children even if you do not notice any signs or symptoms.

Directions

- find right dose on chart
- if possible, use weight to dose; otherwise, use age
- if needed, repeat dose every 4 hours
- do not use more than 5 times in 24 hours

Weight | Age | Dose
under 24 lbs | under 2 years | ask a doctor
24 to 35 lbs | 2 to 3 years | 1 teaspoon (5 mL)
36 to 47 lbs | 4 to 5 years | 1 ½ teaspoons (7.5 mL)
48 to 59 lbs | 6 to 8 years | 2 teaspoons (10 mL)
60 to 71 lbs | 9 to 10 years | 2 ½ teaspoons (12.5 mL)
72 to 95 lbs | 11 years | 3 teaspoons (15 mL)

Other information

store at room temperature 15°-30°C (59°-86°F)

Inactive ingredients

artificial cherry flavor, benzoic acid, citric acid, D&C Red #33, FD&C Red #40, glycerin, polyethylene glycol 1450, propylene glycol, purified water, sodium benzoate, sorbitol solution, sucrose

Questions?

Call 1-888-838-2872, weekdays, 8 AM - 5 PM Eastern Time

PRINCIPAL DISPLAY PANEL

ACETAMINOPHEN

ORAL SOLUTION USP

160 mg/5 mL

PAIN RELIEVER - FEVER REDUCER

Alcohol-Free
Aspirin-Free
Saccharin-Free
Cherry-Flavored

EACH TEASPOON (5 mL) CONTAINS:
Acetaminophen USP 160 mg

TAMPER-EVIDENT: Do not use this product if
inner foil seal over the mouth of the bottle
is cut, torn, broken or missing.

THIS PACKAGE FOR HOUSEHOLDS
WITHOUT YOUNG CHILDREN

Distributed by:
GOLDLINE LABORATORIES, INC.
Sellersville, PA 18960
Dist. 1990 0809REV 71

Relabeling of "Additional Barcode Label" by:
Physicians Total Care, Inc.
Tulsa, OK 74146

NDC 54868-1791-0
TAMPER-EVIDENT

ONE PINT (473 mL)